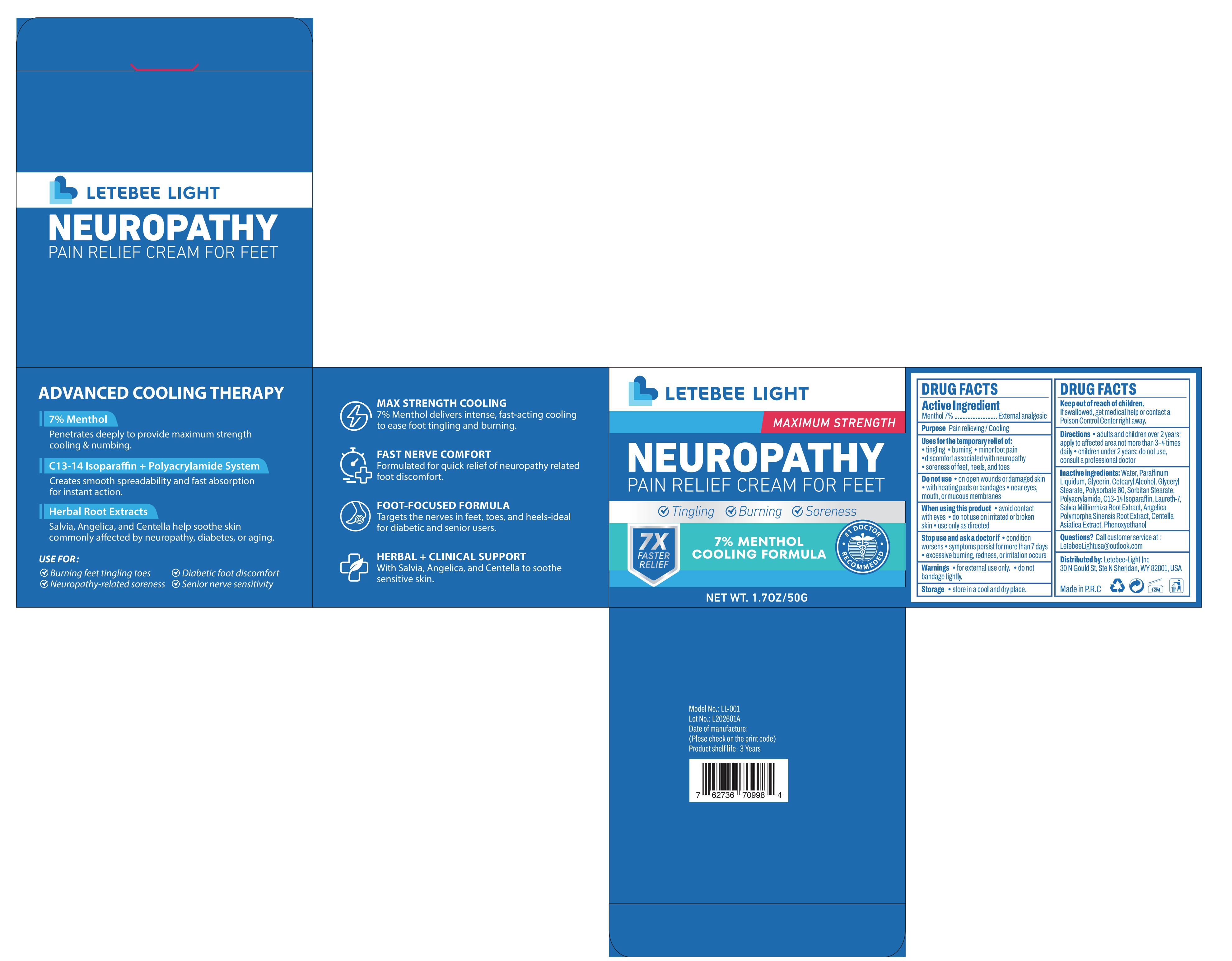 DRUG LABEL: LETEBEE LIGHT neuropathy pain relief cream for feet
NDC: 83566-560 | Form: CREAM
Manufacturer: Guangdong Aimu Biological Technology Co., Ltd
Category: otc | Type: HUMAN OTC DRUG LABEL
Date: 20251211

ACTIVE INGREDIENTS: MENTHOL 7 g/100 g
INACTIVE INGREDIENTS: PHENOXYETHANOL; GLYCERIN; GLYCERYL STEARATE; PARAFFINUM LIQUIDUM; CENTELLA ASIATICA; C13-14 ISOPARAFFIN; SALVIA MILTIORRHIZA ROOT; POLYSORBATE 60; LAURETH-7; POLYACRYLAMIDE (10000 MW); WATER; CETEARYL ALCOHOL; ANGELICA POLYMORPHA ROOT; SORBITAN STEARATE

LETEBEE LIGHT neuropathy pain relief cream for feet

Active Ingredients

Menthol 7%

Purpose

Pain relieving/Cooling

Uses

Uses for the temporary relief of:tingling burning ·minor foot pain discomfort associated with neuropathy soreness of feet, heels, and toes

Warnings

for external use only. do not bandage tightly.

Stop Use

Stop use and ask a doctor if condition worsens symptoms persist for more than 7 days excessive burning,redness, or irritation occurs

Do Not Use

On open wounds or damaged skin with heating pads or bandages near eyes.mouth, or mucous membranes

When Using

Avoid contact with eyes

Do not use on irritated or broken skin *

Use only as directed

Keep Out Of Reach Of Children

If swallowed, get medical help or contact a Poison Control Center right away.

Dosage & administration

Get an appropriate amount of Pain Relief Cream with finger and spread evenly on skin.

Inactive ingredients

WATER 75.35%
PARAFFINUM LIQUIDUM 7%
GLYCERIN 3%
CETEARYL ALCOHOL 2%
GLYCERYL STEARATE 2%
POLYSORBATE 60 1%
SORBITAN STEARATE 1%
POLYACRYLAMIDE 0.25%
C13-14 ISOPARAFFIN 0.25%
LAURETH-7 0.2%
SALVIA MILTIORRHIZA ROOT EXTRACT 0.2%
ANGELICA POLYMORPHA SINENSIS ROOT EXTRACT 0.2%
CENTELLA ASIATICA EXTRACT 0.2%
PHENOXYETHANOL 0.35%